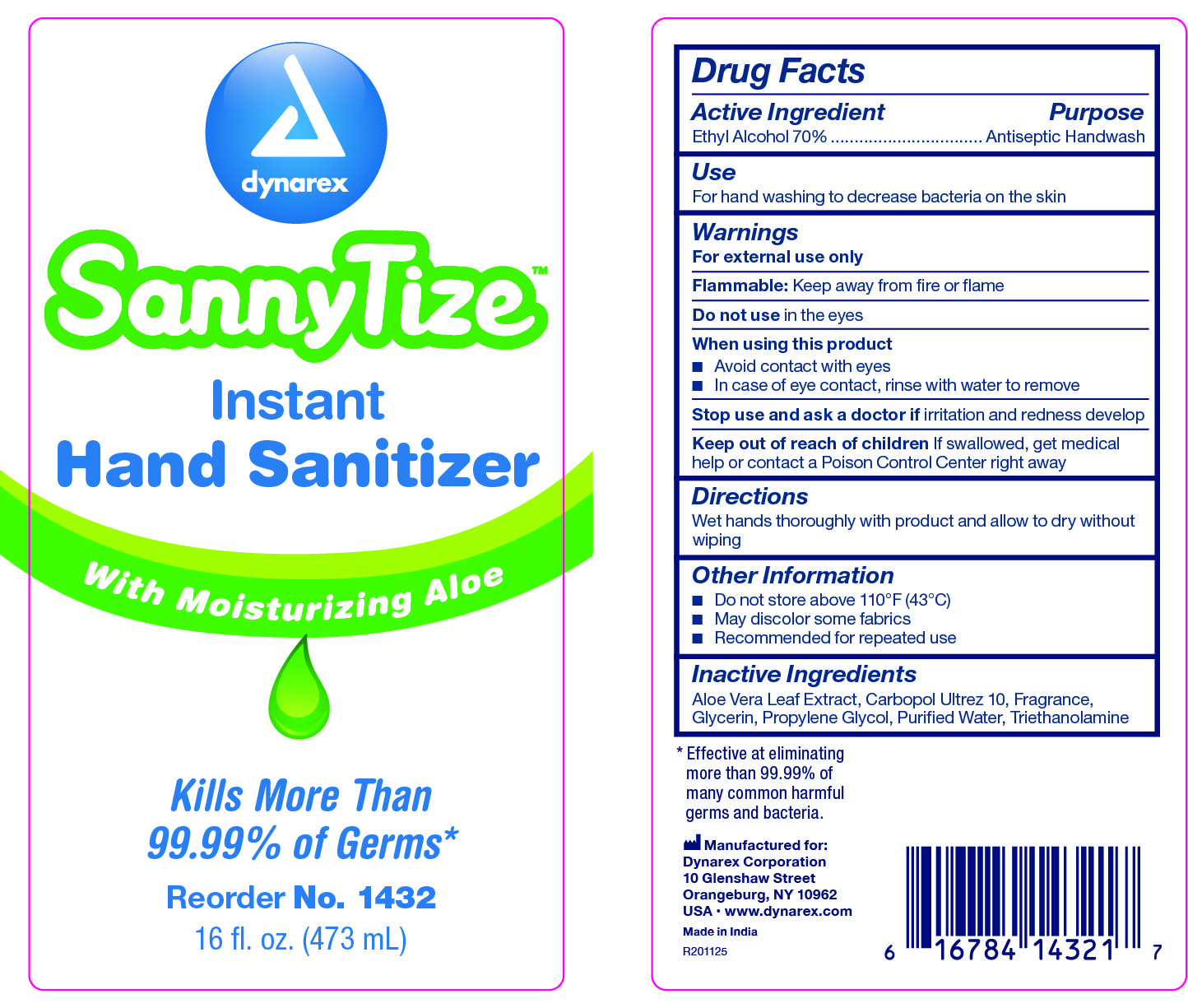 DRUG LABEL: SannyTize Hand Sanitizer
NDC: 67777-317 | Form: GEL
Manufacturer: Dynarex Corporation
Category: otc | Type: HUMAN OTC DRUG LABEL
Date: 20210319

ACTIVE INGREDIENTS: ALCOHOL 0.62 mL/1 mL
INACTIVE INGREDIENTS: WATER; GLYCERIN; PROPYLENE GLYCOL; CARBOMER COPOLYMER TYPE A; TROLAMINE; ALOE VERA LEAF

1427 Dynarex SannyTize Hand Sanitizer NDC 67777-317-01
1428 Dynarex SannyTize Hand Sanitizer NDC 67777-317-02
1429 Dynarex SannyTize Hand Sanitizer NDC 67777-317-03
1431 Dynarex SannyTize Hand Sanitizer NDC 67777-317-04
1432 Dynarex SannyTize Hand Sanitizer NDC 67777-317-05
1433 Dynarex SannyTize Hand Sanitizer NDC 67777-317-06

ACTIVE INGREDIENT

Active Ingredient Purpose

Ethyl Alcohol 0.62% Antiseptic Handwash

WARNINGS

- For external use only
- Flammable, keep away from fire and flame
- Do not use in or near the eyes
- When using this product avoid contact with eyes. In case of eye contact, rinse with water to remove.
- Stop use and ask a doctor if irritation andredness develops

PURPOSE

An antiseptic handwash.

INDICATIONS & USAGE

Cleaning and antiseptic cleansing of hands and skin.

DOSAGE & ADMINISTRATION

- Wet hands thoroughly with product and allow to dry without wiping

KEEP OUT OF REACH OF CHILDREN, if swallowed get medical help or contact a Poison Control Center right away.

INACTIVE INGREDIENTS

Inactive ingredients: Water, Glycerin, Propylene glycol, Carbomer, Triethanolamine, Aloe barbadensis juice, Fragrance